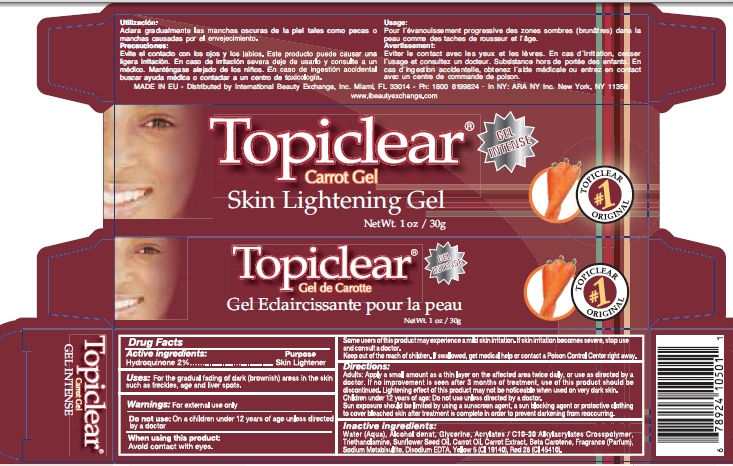 DRUG LABEL: Topiclear Carrot 
NDC: 66129-045 | Form: GEL
Manufacturer: International Beauty Exchange Inc
Category: otc | Type: HUMAN OTC DRUG LABEL
Date: 20110223

ACTIVE INGREDIENTS: Hydroquinone .6 g/30 g
INACTIVE INGREDIENTS: WATER; ALCOHOL; GLYCERIN; CARBOMER COPOLYMER TYPE A; TROLAMINE; SUNFLOWER OIL; CARROT SEED OIL; CARROT; BETA CAROTENE; EDETATE DISODIUM; FD&C YELLOW NO. 5; D&C RED NO. 28

Drug facts

ACTIVE INGREDIENT

Hydroquinone 2%

WARNINGS

For external use only.

DO NOT USE

On children under 12 years of age unless directed by a doctor

WHEN USING

Avoid contact with eyes.

INACTIVE INGREDIENT

Water, Alcohol denat, glycerine, acrylates/ C10-30 Akylacrylates Crosspolymer...

KEEP OUT OF REACH OF CHILDREN

If swallowed, get medical help or contact a Poison Control Center right away.

PURPOSE

Skin Lightener

INDICATIONS AND USAGE

Enter section text here

DOSAGE AND ADMINISTRATION

Apply a small amount as a thin layer on the affected area twice daily